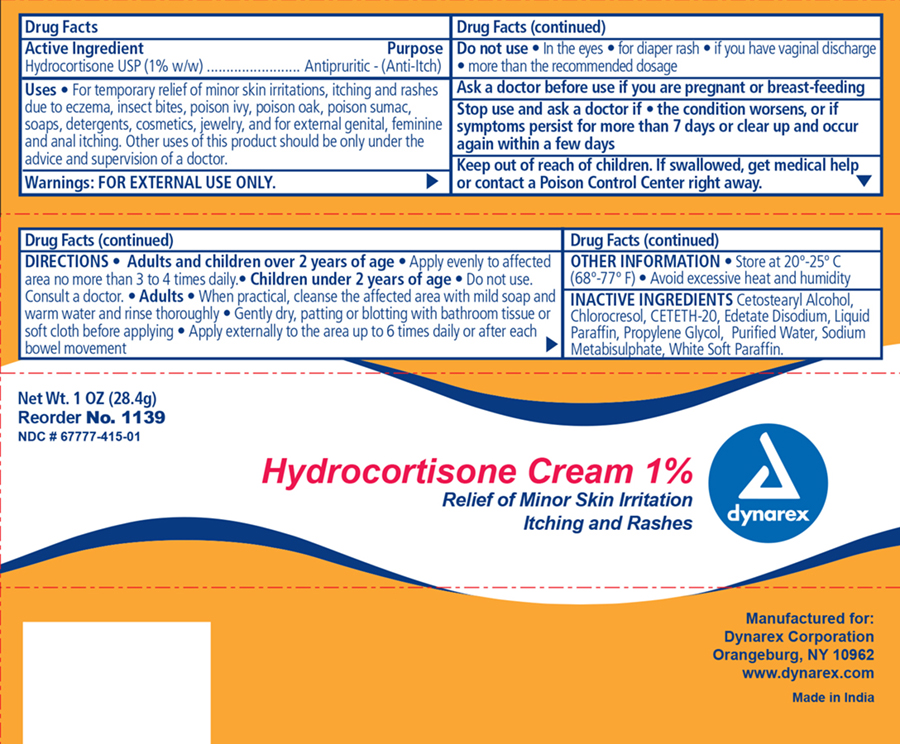 DRUG LABEL: Hydrocortisone
NDC: 67777-415 | Form: CREAM
Manufacturer: Dynarex Corporation
Category: otc | Type: HUMAN OTC DRUG LABEL
Date: 20160504

ACTIVE INGREDIENTS: HYDROCORTISONE 1 g/100 g
INACTIVE INGREDIENTS: PROPYLENE GLYCOL; WATER; ceteth-20; CETOSTEARYL ALCOHOL; EDETATE DISODIUM; MINERAL OIL; SODIUM METABISULFITE; PETROLATUM

Dynarex Hydrocortisone Cream 1%

Active ingredient Purpose

Hydrocortisone 1% Antipruritic (anti-itch)

Warnings

For external use only

Purpose

For temporary relief of:

- minor skin irritations

Itches and rashes due to:

- eczema
- insect bites
- poison ivy
- poison oak
- poison sumac
- soaps
- detergents
- cosmetics
- jewelry

and for external itching of:

- genital
- feminine and
- anal itching

Do Not Use:

- in the eyes
- longer than 1 week unless directed by a physician
- for diaper rash
- if you have vaginal discharge
- more than recommended daily dosage unless directed by a doctor
- in the rectum using fingers or any other mechanical device or applicator

Stop use and ask a physician if:

- the condition persists or gets worse
- symptoms clear up and appear again within a few days
- you are pregnant or breast feeding

Keep Out Of Reach of Children

- if swallowed, get medical help or contact a Poison Control Center right away.

Directions:

Adults and children 2 years of age:

- apply evenly to affected area no more than 3 or 4 times daily.

Children under 2 years of age:

- Do not use
- consult a physician

Adults:

- when practical, cleanse the affected area with mild soap and warm water and rinse thoroughly
- gently dry, patting and blotting with bathroom tissue or soft cloth before applying
- apply externally to the area up to 6 times daily or after each bowel movement

Inactive ingredients:

Cetomacrogol 1000, cetostearyl alcohol, chlorocresol, edetate disodium, liquid paraffin, propylene glycol, sodium betabisulphate, white soft paraffin, water (purified)

Other information:

- store at 20 deg. to 25 deg. C (68 deg. - 77 deg. F)
- avoid excessive heat and humidity

INDICATIONS AND USAGE

For temporary relief of minor skin irritations and external itching.

PACKAGE LABEL

Principal Display Panel

Dynarex Hydrocortisone Items 1137 and 1139

Hydro1139.jpg